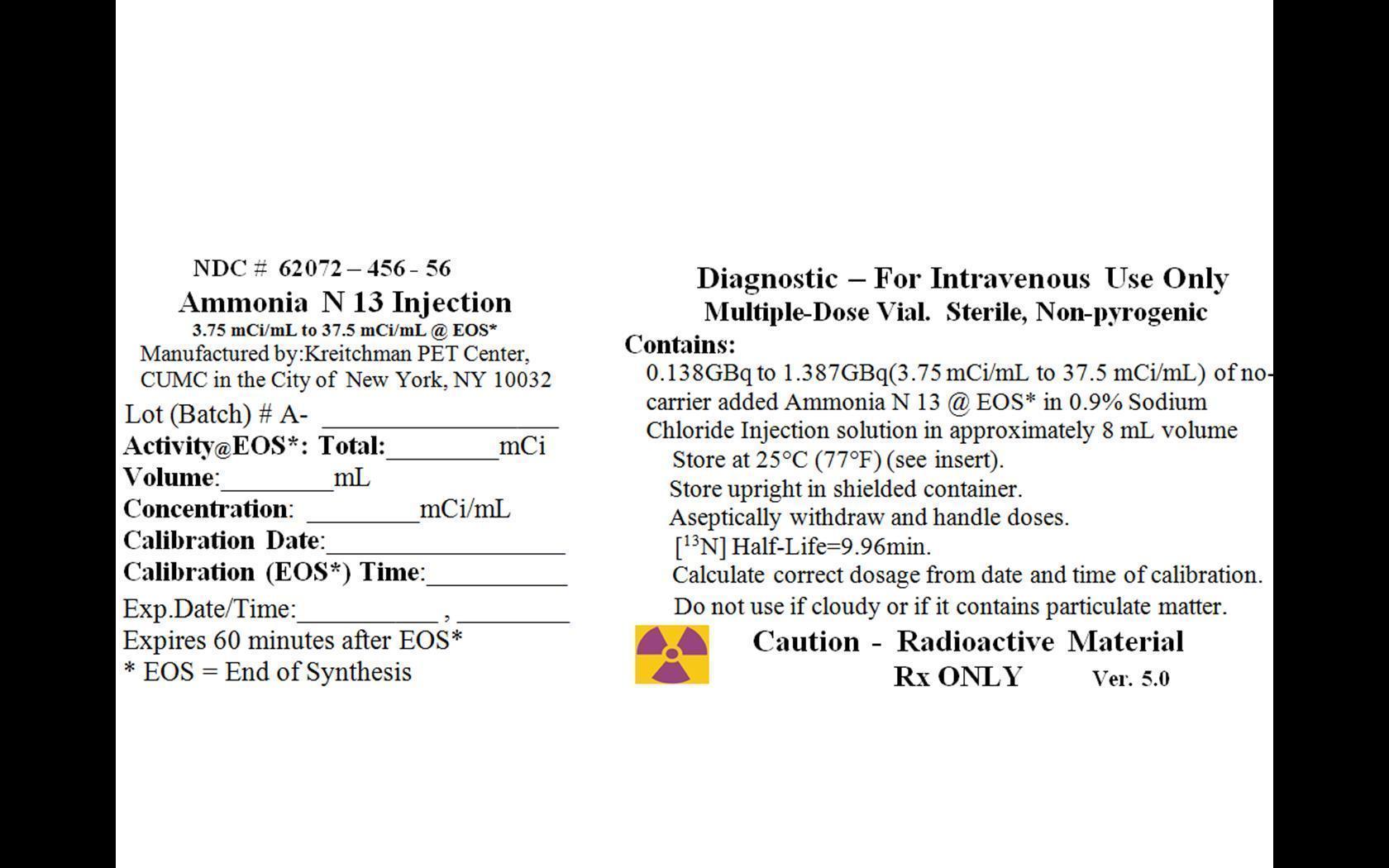 DRUG LABEL: Ammonia
NDC: 62072-456 | Form: INJECTION
Manufacturer: Kreitchman PET Center
Category: prescription | Type: HUMAN PRESCRIPTION DRUG LABEL
Date: 20260127

ACTIVE INGREDIENTS: AMMONIA N-13 37.5 mCi/1 mL

HIGHLIGHTS OF PRESCRIBING INFORMATION

These highlights do not include all the information needed to use Ammonia N 13 Injection safely and effectively. See full prescribing information for Ammonia N 13 Injection.
Ammonia N 13 Injection for intravenous use
Initial U.S. Approval: 2007

6 ADVERSE REACTIONS

No adverse reactions have been reported for Ammonia N 13 Injection based on a review of the published literature, publicly available reference sources, and adverse drug reaction reporting system(6).

To report SUSPECTED ADVERSE REACTIONS, contact Kreitchman PET Center at 212-305-0081 or FDA at 1-800-FDA-1088 or www.fda.gov/medwatch.

FULL PRESCRIBING INFORMATION

6 ADVERSE REACTIONS

No adverse reactions have been reported for Ammonia N 13 Injection based on a review of the published literature, publicly available reference sources, and adverse drug reaction reporting systems. However, the completeness of these sources is not known.

Manufactured by: Kreitchman PET Center, 722 W 168th Street, R-1 Level Room 110, New York, NY 10032

Distributed by: Kreitchman PET Center, 722 W 168th Street, R-1 Level Room 110, New York, NY 10032